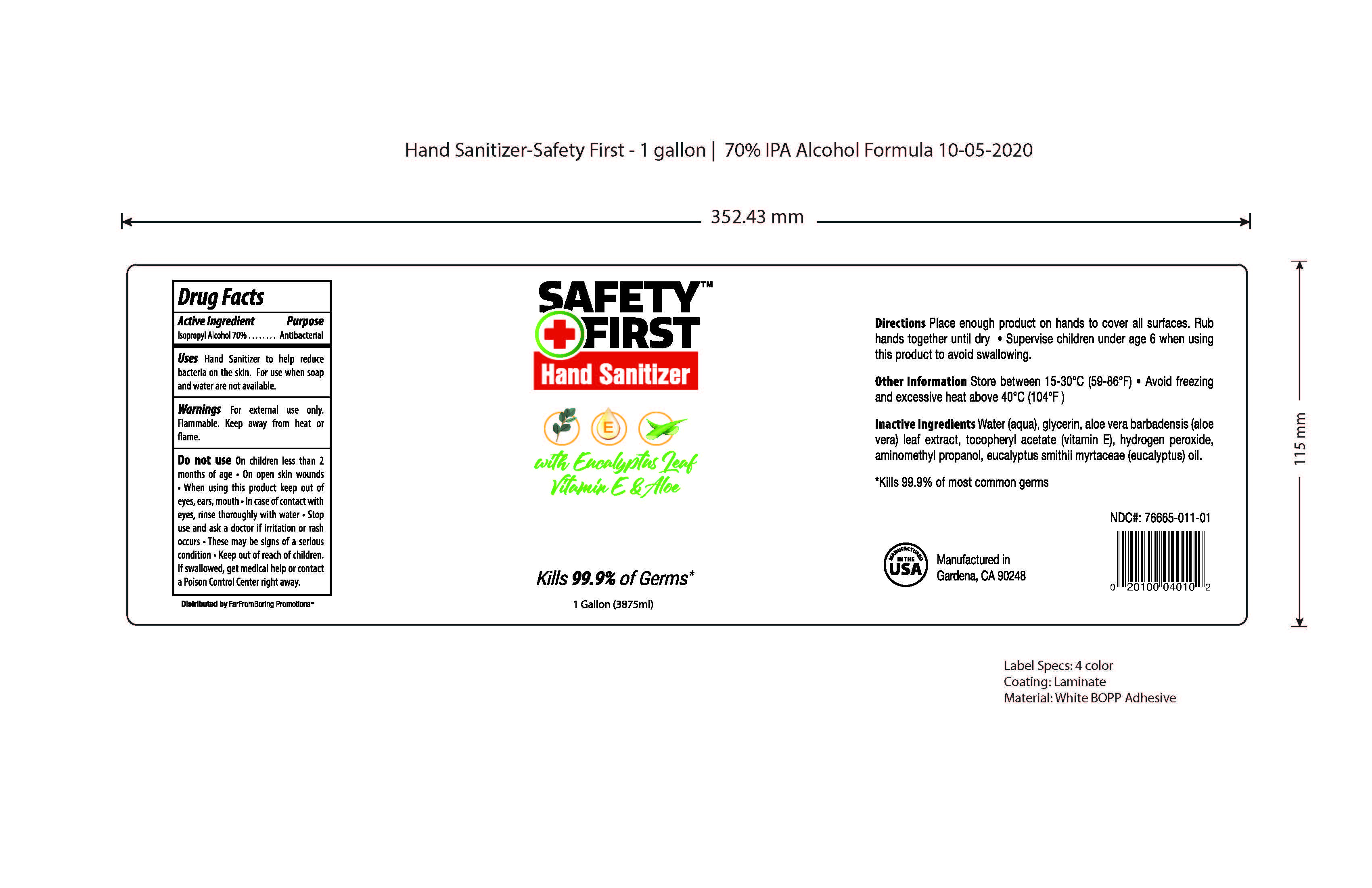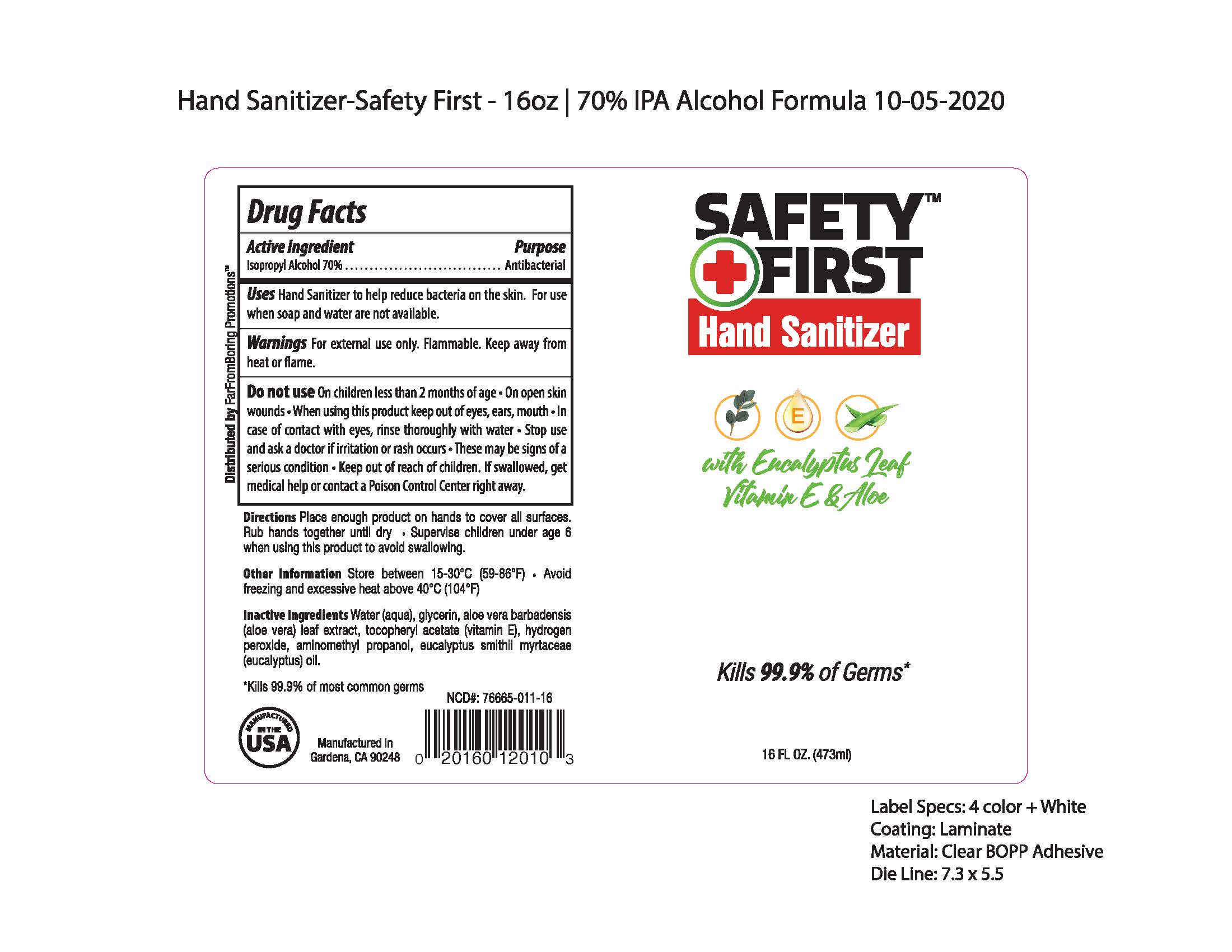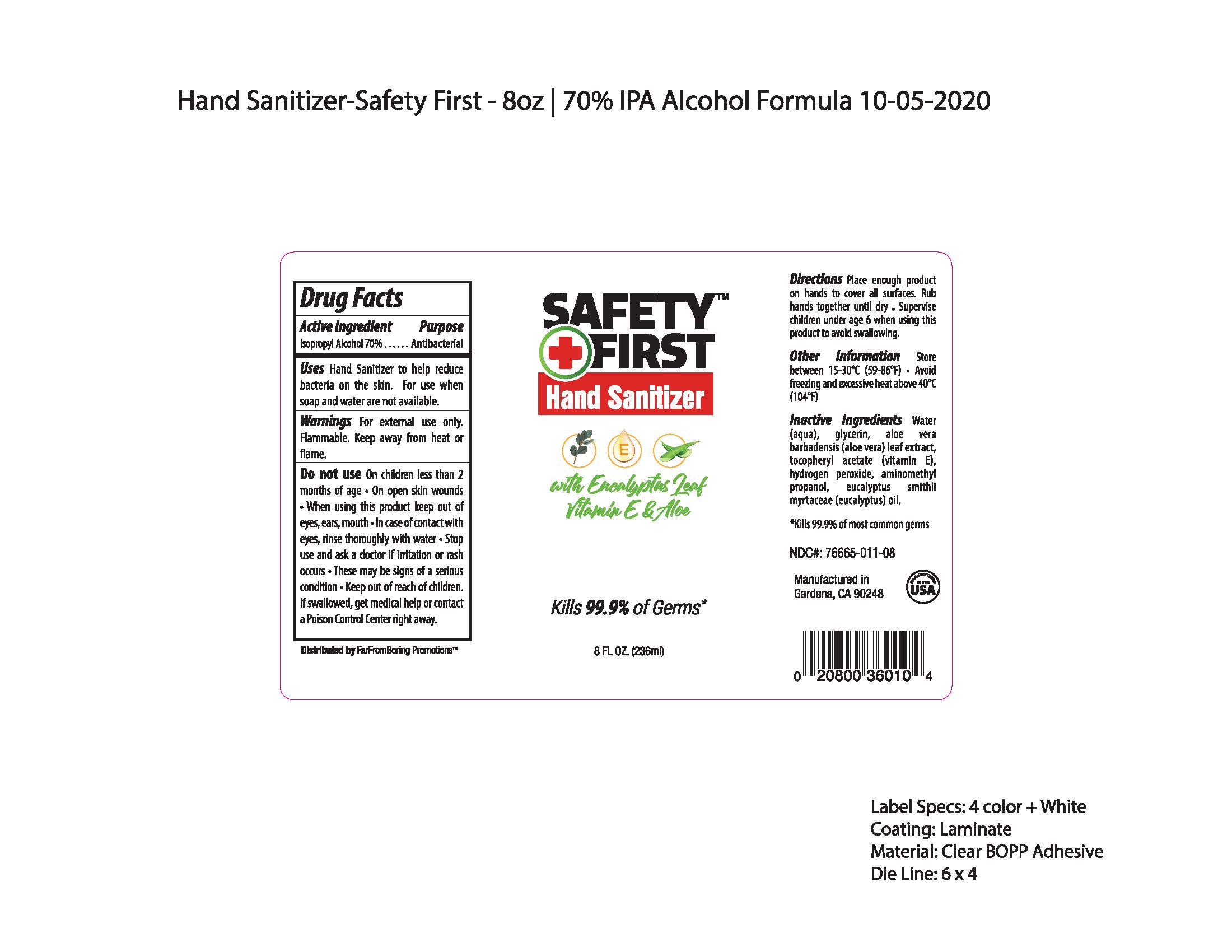 DRUG LABEL: Safety First
NDC: 76665-011 | Form: LIQUID
Manufacturer: Clean Beauty Concepts
Category: otc | Type: HUMAN OTC DRUG LABEL
Date: 20201011

ACTIVE INGREDIENTS: ISOPROPYL ALCOHOL 70 mL/100 mL
INACTIVE INGREDIENTS: EUCALYPTUS SMITHII OIL 0.3 mL/100 mL; GLYCERIN 1.45 mL/100 mL; HYDROGEN PEROXIDE 0.125 mL/100 mL; CARBOMER INTERPOLYMER TYPE A (55000 CPS) 0.2 mL/100 mL; ALOE VERA LEAF 0.1 mL/100 mL; AMINOMETHYLPROPANOL 0.06 mL/100 mL; WATER 27.665 mL/100 mL; .ALPHA.-TOCOPHEROL ACETATE, D- 0.1 mL/100 mL

The sanitizer wipes is manufactured using only the following United States Pharmacopoeia (USP) grade ingredients:

1. Alcohol (Isopropyl alcohol) (USP or Food Chemical Codex (FCC) grade) (75%, volume/volume (v/v)) in an aqueous solution denatured according to Alcohol and Tobacco Tax and Trade Bureau regulations in 27 CFR part 20.
2. Glycerol
3. Hydrogen peroxide
4. Sterile distilled water or boiled cold water. (27.465%)
5. Fragrance (Parfum)
6. Aloe vera leaf extract
7. Tocopheryl Acetate (Vitamin E)
8. Aminomethyl Propanol

Active Ingredient(s)

Isopropyl Alcohol 70% v/v. Purpose: Antiseptic

Purpose

Antibacterial

Use

Hand Sanitizer to help reduce bacteria on the skin. For use when soap and water are not available.

Warnings

For external use only. Flammable. Keep away from heat or flame

Do not use

- on children less than 2 months of age
- on open skin wounds

When using this product keep out of eyes, ears, and mouth. In case of contact with eyes, rinse eyes thoroughly with water.
Stop use and ask a doctor if irritation or rash occurs. These may be signs of a serious condition.
Keep out of reach of children. If swallowed, get medical help or contact a Poison Control Center right away.

Stop use and ask a doctor if irritation or rash occurs. These may be signs of a serious condition.

Keep out of reach of children. If swallowed, get medical help or contact a Poison Control Center right away.

Directions

- Place enough product on hands to cover all surfaces. Rub hands together until dry
- Supervise children under age 6 when using this product to avoid swallowing

Other information

- Store between 15-30C (59-86F)
- Avoid freezing and excessive heat above 40C (104F)

Inactive ingredients

water(aqua), glycerin, aloe vera barbadensis (aloe vera) leaf extract, tocopheryl acetate (Vitamine E), hydrogen peroxide, Aminomethyl Propanol, fragrance(parfum)

Package Label - Principal Display Panel

3875 mL NDC: 76665-011-01

473 mL NDC: 76665-011-16

236mL NDC: 76665-011-08